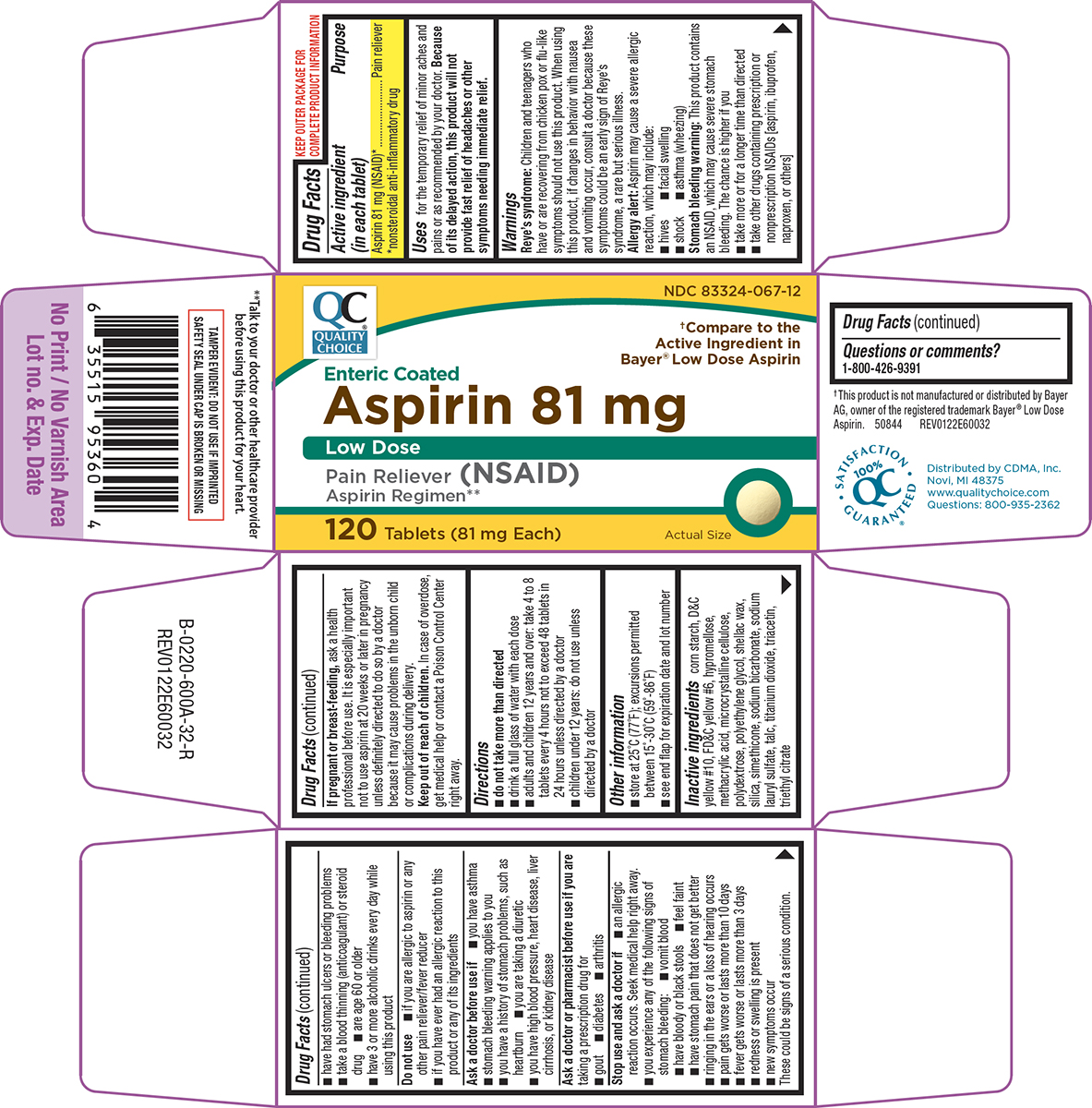 DRUG LABEL: Aspirin
NDC: 83324-067 | Form: TABLET, DELAYED RELEASE
Manufacturer: Chain Drug Marketing Association, Inc.
Category: otc | Type: HUMAN OTC DRUG LABEL
Date: 20260206

ACTIVE INGREDIENTS: ASPIRIN 81 mg/1 1
INACTIVE INGREDIENTS: STARCH, CORN; D&C YELLOW NO. 10; FD&C YELLOW NO. 6; HYPROMELLOSE, UNSPECIFIED; METHACRYLIC ACID; MICROCRYSTALLINE CELLULOSE; POLYDEXTROSE; POLYETHYLENE GLYCOL, UNSPECIFIED; SHELLAC; SILICON DIOXIDE; DIMETHICONE; WATER; SODIUM BICARBONATE; SODIUM LAURYL SULFATE; TALC; TITANIUM DIOXIDE; TRIACETIN; TRIETHYL CITRATE

Quality Choice 44-600A-NDC 83324-067

Active ingredient (in each tablet)

Aspirin 81 mg (NSAID)*
*nonsteroidal anti-inflammatory drug

Purpose

Pain reliever

Uses

for the temporary relief of minor aches and pains or as recommended by your doctor. Because of its delayed action, this product will not provide fast relief of headaches or other symptoms needing immediate relief.

Warnings

Reye’s syndrome: Children and teenagers who have or are recovering from chicken pox or flu-like symptoms should not use this product. When using this product, if changes in behavior with nausea and vomiting occur, consult a doctor because these symptoms could be an early sign of Reye's syndrome, a rare but serious illness.

Allergy alert: Aspirin may cause a severe allergic reaction, which may include:

- hives
- facial swelling
- shock
- asthma (wheezing)

Stomach bleeding warning: This product contains an NSAID, which may cause severe stomach bleeding. The chance is higher if you

- take more or for a longer time than directed
- take other drugs containing prescription or nonprescription NSAIDs [aspirin, ibuprofen, naproxen, or others]
- have had stomach ulcers or bleeding problems
- take a blood thinning (anticoagulant) or steroid drug
- are age 60 or older
- have 3 or more alcoholic drinks every day while using this product

Do not use

- if you are allergic to aspirin or any other pain reliever/fever reducer
- if you have ever had an allergic reaction to this product or any of its ingredients

Ask a doctor before use if

- you have asthma
- stomach bleeding warning applies to you
- you have a history of stomach problems, such as heartburn
- you are taking a diuretic
- you have high blood pressure, heart disease, liver cirrhosis, or kidney disease

Ask a doctor or pharmacist before use if you are

taking a prescription drug for

- gout
- diabetes
- arthritis

Stop use and ask a doctor if

- an allergic reaction occurs. Seek medical help right away.
- you experience any of the following signs of stomach bleeding:
  - vomit blood
  - have bloody or black stools
  - feel faint
  - have stomach pain that does not get better
- ringing in the ears or a loss of hearing occurs
- pain gets worse or lasts more than 10 days
- fever gets worse or lasts more than 3 days
- redness or swelling is present
- new symptoms occur

These could be signs of a serious condition.

If pregnant or breast-feeding,

ask a health professional before use. It is especially important not to use aspirin at 20 weeks or later in pregnancy unless definitely directed to do so by a doctor because it may cause problems in the unborn child or complications during delivery.

Keep out of reach of children.

In case of overdose, get medical help or contact a Poison Control Center right away.

Directions

- do not take more than directed
- drink a full glass of water with each dose
- adults and children 12 years and over: take 4 to 8 tablets every 4 hours not to exceed 48 tablets in 24 hours unless directed by a doctor
- children under 12 years: do not use unless directed by a doctor

Other information

- store at 25°C (77°F); excursions permitted between 15°-30°C (59°-86°F)
- see end flap for expiration date and lot number

Inactive ingredients

corn starch, D&C yellow #10, FD&C yellow #6, hypromellose, methacrylic acid, microcrystalline cellulose, polydextrose, polyethylene glycol, shellac wax, silica, simethicone, sodium bicarbonate, sodium lauryl sulfate, talc, titanium dioxide, triacetin, triethyl citrate

Questions or comments?

1-800-426-9391

Principal Display Panel

QC®
QUALITY
CHOICE

NDC 83324-067-12

†Compare to the
Active Ingredient in
Bayer® Low Dose Aspirin

Enteric Coated
Aspirin 81 mg
Low Dose
Pain Reliever (NSAID)
Aspirin Regimen**

120 Tablets (81 mg Each)

Actual Size

**Talk to your doctor or other healthcare provider
before using this product for your heart.

TAMPER EVIDENT: DO NOT USE IF IMPRINTED
SAFETY SEAL UNDER CAP IS BROKEN OR MISSING

†This product is not manufactured or distributed by Bayer
AG, owner of the registered trademark Bayer ® Low Dose
Aspirin. 50844 REV0122E60032

Distributed by CDMA, Inc.
Novi, MI 48375
www.qualitychoice.com
Questions: 800-935-2362

Quality Choice 44-600A